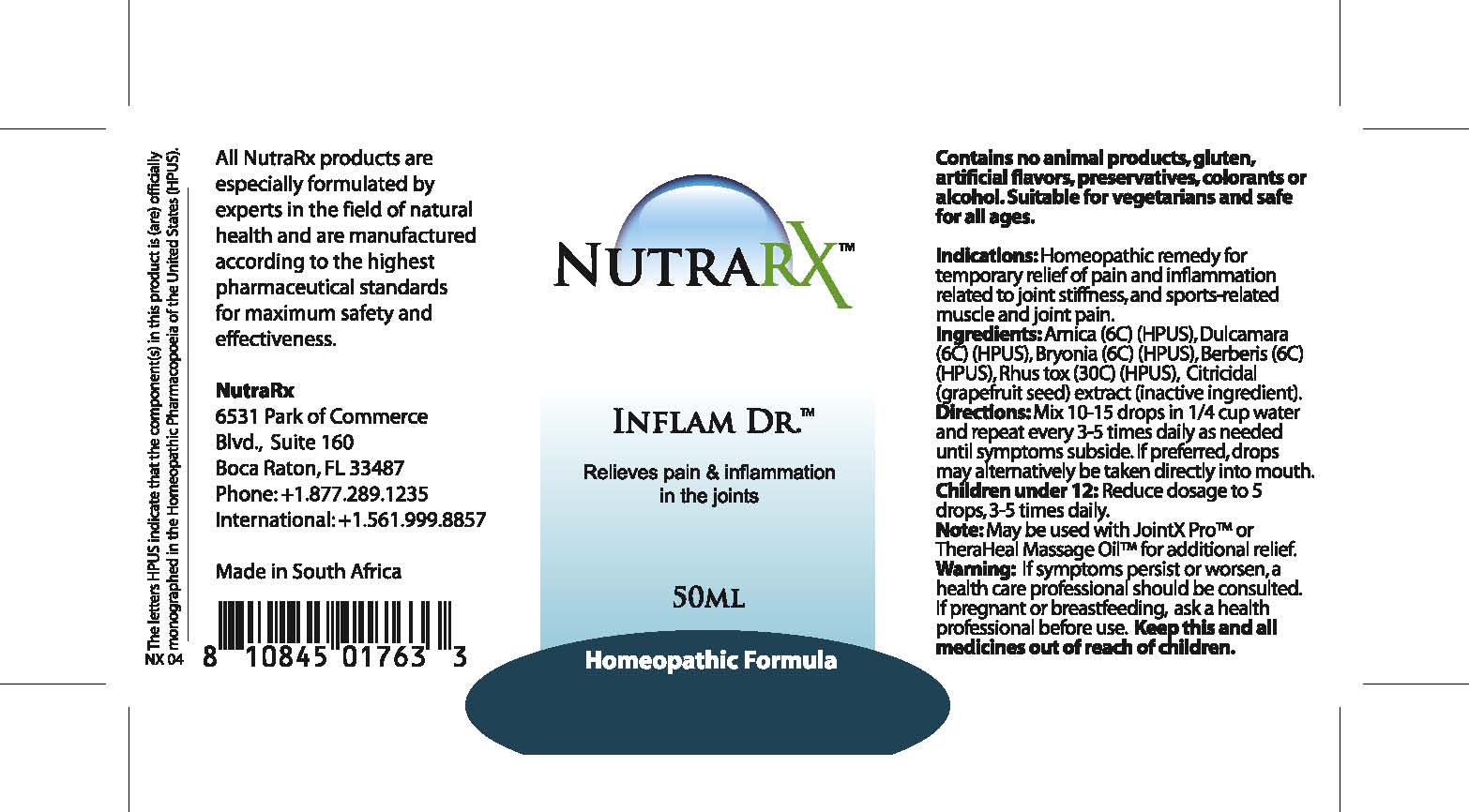 DRUG LABEL: NutraRX Inflam Dr.
NDC: 68647-193 | Form: TINCTURE
Manufacturer: Feelgood Health
Category: homeopathic | Type: HUMAN OTC DRUG LABEL
Date: 20100908

ACTIVE INGREDIENTS: ARNICA MONTANA 6 [hp_C]/40 mL; SOLANUM DULCAMARA TOP 6 [hp_C]/40 mL; BRYONIA ALBA ROOT 6 [hp_C]/40 mL; BERBERIS VULGARIS ROOT BARK 6 [hp_C]/40 mL; TOXICODENDRON PUBESCENS LEAF 30 [hp_C]/40 mL
INACTIVE INGREDIENTS: CITRUS PARADISI SEED 01.25 mL/50 mL; WATER 49.486 mL/50 mL

NUTRA RX INFLAM DR

PURPOSE

Relieves pain and inflammation in the joints

INDICATIONS AND USAGE

Indications: Homeopathic remedy for temporary relief of pain and inflammation related to joint stiffness, and sports-related muscle and joint pain.

DOSAGE AND ADMINISTRATION

Directions: Mix 10-15 drops in 1/4 cup water and repeat every 3-5 times daily as needed until symptoms subside. If preferred, drops may alternatively be taken directly into mouth. Children under 12: Reduce dosage to 5 drops, 3-5 times daily.

GENERAL PRECAUTIONS

Warning: If symptoms persist or worsen, a health care professional should be consulted. Keep this and all medicines out of reach of children.

ACTIVE INGREDIENT

Ingredients: Arnica (6C) (HPUS), Dulcamara (6C) (HPUS), Bryonia (6C) (HPUS), Berberis (6C) (HPUS), Rhus tox (30C) (HPUS)

Citricidal (grapefruit seed) extract (inactive ingredient).

PREGNANCY

If pregnant or breastfeeding, ask a health professional before use.

WARNINGS

Contains no animal products, gluten, artificial flavors, preservatives, colorants or alcohol. Suitable for vegetarians and safe for all ages.

PATIENT COUNSELING INFORMATION

All Native Remedies health products are especially formulated by experts in the field of natural health and are manufactured according to the highest pharmaceutical standards for maximum safety and effectiveness. For more information, visit us at www.nativeremedies.com

Distributed by

Native Remedies, LLC

6531 Park of Commerce Blvd.

Suite 160

Boca Raton, FL 33487

Phone: 1.877.289.1235

International: + 1.561.999.8857

The letters HPUS indicate that the component(s) in this product is (are) officially monographed in the Homeopathic Pharmacopoeia of the United States.

KEEP OUT OF REACH OF CHILDREN

Keep this and all medicines out of reach of children.